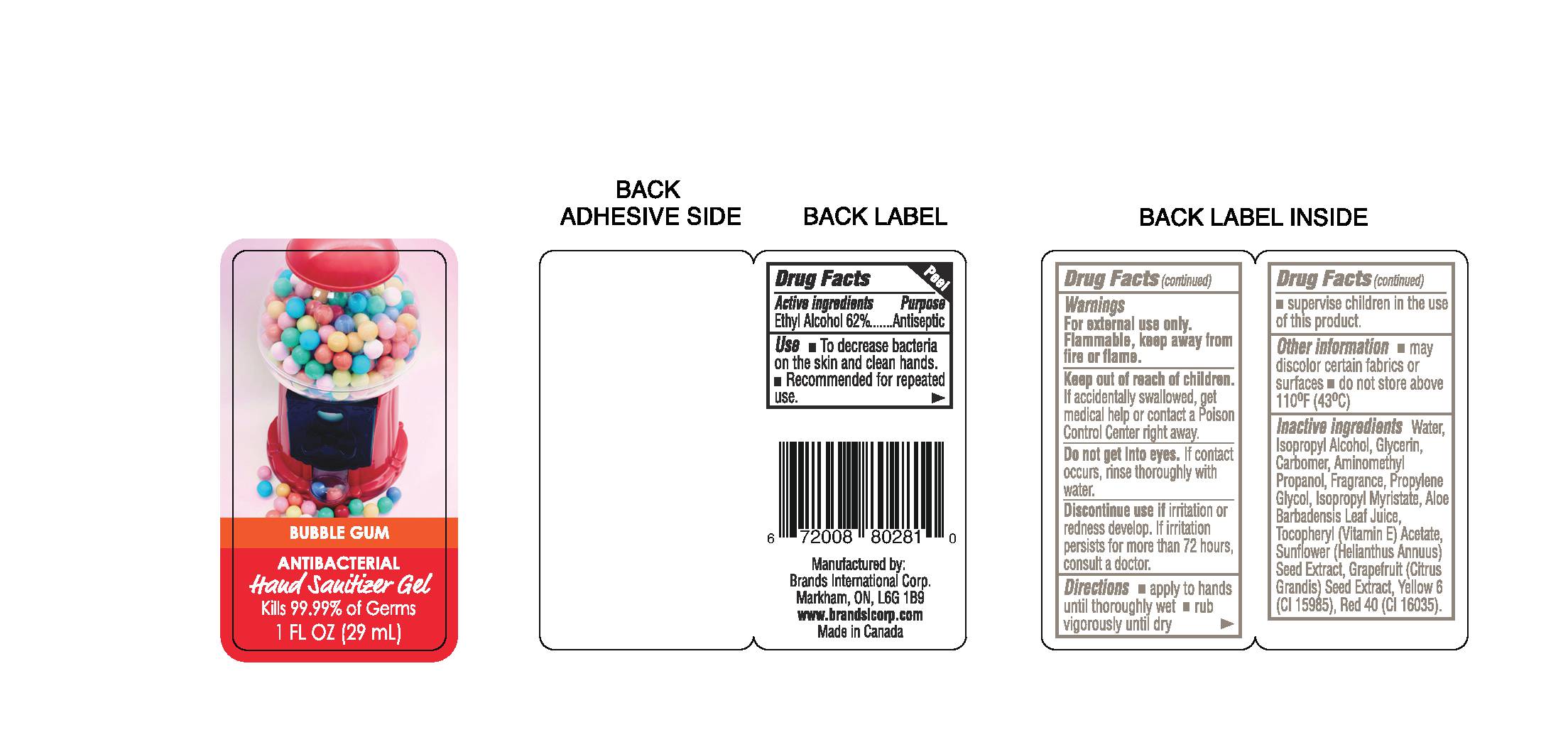 DRUG LABEL: Bubble Gum
NDC: 50157-116 | Form: GEL
Manufacturer: Brands Internation Corp
Category: otc | Type: HUMAN OTC DRUG LABEL
Date: 20150110

ACTIVE INGREDIENTS: ALCOHOL 620 mL/1000 mL
INACTIVE INGREDIENTS: FD&C RED NO. 40; ISOPROPYL ALCOHOL; GLYCERIN; CARBOMER 940; AMINOMETHYLPROPANOL; PROPYLENE GLYCOL; ISOPROPYL MYRISTATE; ALOE VERA LEAF; .ALPHA.-TOCOPHEROL ACETATE, DL-; SUNFLOWER SEED; GRAPEFRUIT SEED OIL; FD&C YELLOW NO. 6; WATER

Active Ingredient - Ethyl Alcohol 62%

Purpose - Antiseptic

Use

- to decrease bacteria on the skin and clean hands
- recommeded for repeated use

Warnings

for external use only

Flammable, keep away from fire or flame

KEEP OUT OF REACH OF CHILDREN

Keep out of children. If accidently swallowed, get medical helpor contact a Poison Control Center right away

USER SAFETY WARNINGS

Do not get into eyes, If contact occurs, rinse thoroughly with water

ASK DOCTOR/PHARMACIST

Discontinue Use if irritation or redness develops, If irritation persists for more than 72 hours, consult a doctor

Directions

- apply to hands until thoroughly wet
- rub vigorously until dry
- supervise children in the use of this product

Other information

- may discolor certain fabrics or surfaces
- do not store above 110 F (43 C)

INACTIVE INGREDIENT

Water, Isopropyl Alcohol, Glycerin, Carbomer, Aminomethyl Prpanol, Fragrance, Propylene Glycol, Isopropyl Myristate, Aloe Barbadensis Leaf Juice, Tocopheryl (Vitamin E) Acetate, Sunflower (Heilanthus Annuus) Seed Extract, Grapefruit (Citrus Grandis) Seed Extract, yellow 6 (Cl 15985) Red 40 (Cl 16035)